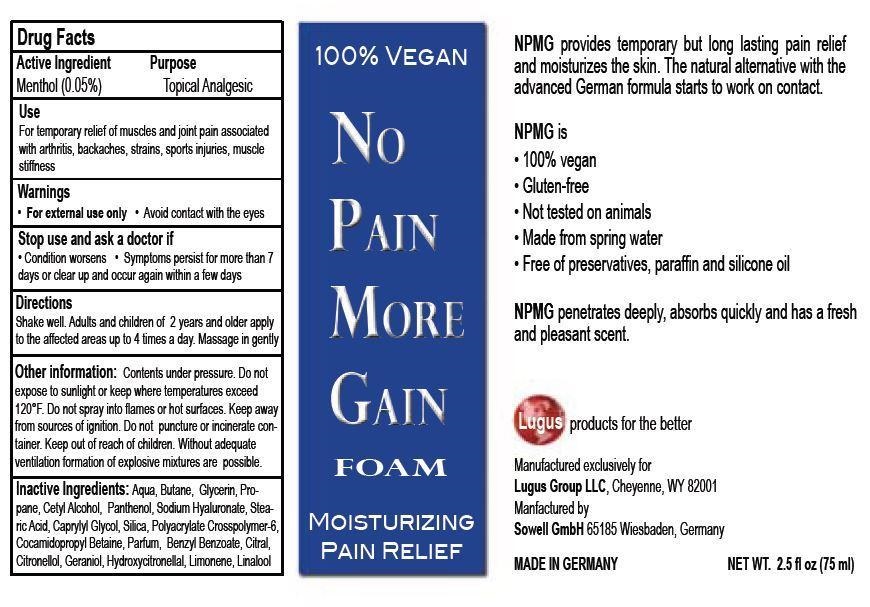 DRUG LABEL: No Pain More Gain
NDC: 71637-002 | Form: AEROSOL, FOAM
Manufacturer: Vema Industrie-Verpackung
Category: otc | Type: HUMAN OTC DRUG LABEL
Date: 20181214

ACTIVE INGREDIENTS: MENTHOL 5 mg/100 mg
INACTIVE INGREDIENTS: WATER; BUTANE; GLYCERIN; PROPANE; CETYL ALCOHOL; PANTHENOL; HYALURONATE SODIUM; STEARIC ACID; CAPRYLYL GLYCOL; SILICON DIOXIDE; COCAMIDOPROPYL BETAINE; BENZYL BENZOATE; CITRAL; .BETA.-CITRONELLOL, (R)-; GERANIOL; HYDROXYCITRONELLAL; LIMONENE, (+)-; LINALOOL, (+)-

Active Ingredient Purpose

Menthol (0.05%) Topical Analgesic

Use

For temporary relief of muscles and joint pain associated with arthritis, backaches, strains, sports injuries, muscle stiffness

Keep out of reach of children.

Directions

Shake Well. Adults and children of 2 years and older apply to the affected areas up to 4 times a day. Massage in gently.

Warnings

For external use only

Avoid contact with the eyes

Stop use and ask a doctor if

- Condition worsens
- Symptoms persist for more than 7 days or clear up and occur again within a few days

INDICATIONS AND USAGE

100% Vegan

No Pain More Gain Foam

Moisturizing Pain Relief

NPMG provides temporary but long lasting pain relief and moisturizes the skin. The natural alternative with the advanced German formula starts to work on contact.

NPMG is

100% vegan

gluten-free

not tested on animals

made from spring water

free of paraben, paraffin and silicone oil

NPMG penetrates deeply, absorbs quickly and has a fresh and pleasant scent.

Lugus products for the better.

Manufactured exclusively for

Lugus Group LLC, Cheyenne, WY 82001

Manufactured by

Sowell GmbH 65185 Wiesbaden, Germany

MADE IN GERMANY

NET WT 2.5 fl oz (75 ml)

Inactive Ingredients

aqua, butane, glycerin, propane, cetyl alcohol, panthenol, sodium hyaluronate, stearic acid, caprylyl glycol, silica, polyacrylate crosspolymer-6, cocamidopropyl betaine, parfum, benzyl benzoate, citral, citronellol, geraniol, hydroxycitronellal, limonene, linalool.

Other Information

Contents under pressure. Do not expose to sunlight or keep where temperatures exceed 120F. Do not spray into flames or hot surfaces. Keep away from sources of ignition. Do not puncture or incinerate container. Keep out of reach of children. Without adequate ventilation formation of explosive mixtures are possible.